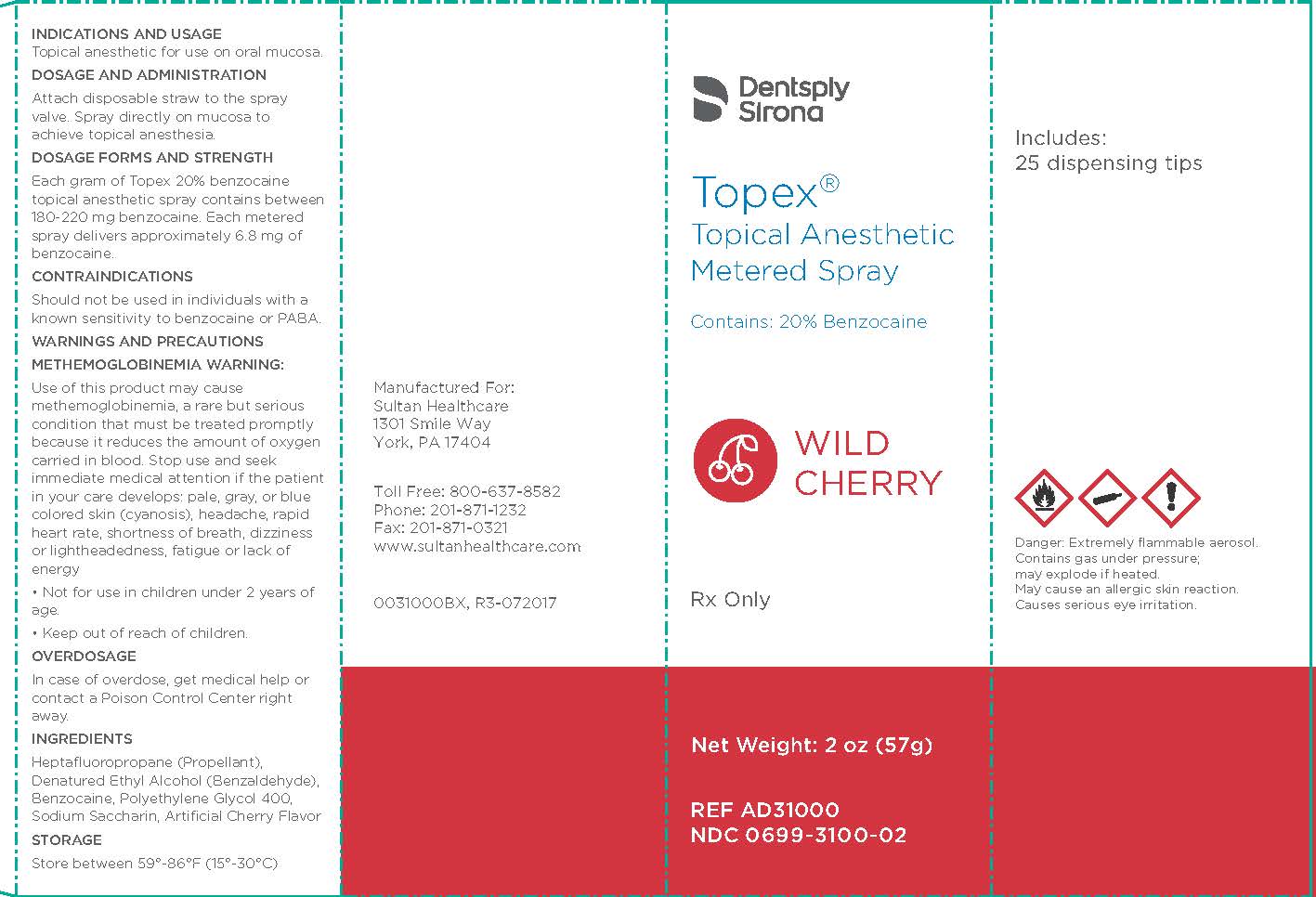 DRUG LABEL: Topex
NDC: 0699-3100 | Form: SPRAY, METERED
Manufacturer: Dentsply LLC. Professional Division Trading as "Sultan Healthcare"
Category: prescription | Type: HUMAN PRESCRIPTION DRUG LABEL
Date: 20240207

ACTIVE INGREDIENTS: BENZOCAINE 220 mg/1 g
INACTIVE INGREDIENTS: SACCHARIN SODIUM; POLYETHYLENE GLYCOL 400; BENZALDEHYDE; APAFLURANE

Topex
Topical Anesthetic
Metered Spray

INDICATIONS AND USAGE

Topical anesthetic for use on oral mucosa

DOSAGE AND ADMINISTRATION

Attach disposable straw to the spray valve. Spray directly on mucosa to achieve topical anesthesia.

DOSAGE FORMS AND STRENGTHS

Each gram of Topex 20% benzocaine topical anesthetic spray contains between 180-220 mg benzocaine. Each metered spray delivers approximately 6.8 mg of benzocaine.

CONTRAINDICATIONS

Should not be used in individuals with a known sensitivity to benzocaine or PABA.

WARNINGS AND PRECAUTIONS

METHEMOGLOBINEMIA WARNING:
Use of this product may cause methemoglobinemia, a rare but serious condition that must be treated promptly because it reduces the amount of oxygen carried in blood. Stop use and seek immediate medical attention if the patient in your care develops:

- pale, gray, or blue colored skin (cyanosis),
- headache,
- rapid heart rate,
- shortness of breath,
- dizziness or lightheadedness,
- fatigue or lack of energy

• Not for use in children under 2 years of age.
• Keep out of reach of children.

OVERDOSAGE

In case of overdose, get medical help or contact a Poison Control Center right away.

STORAGE AND HANDLING

Store between 59°-86°F (15°-30°C).